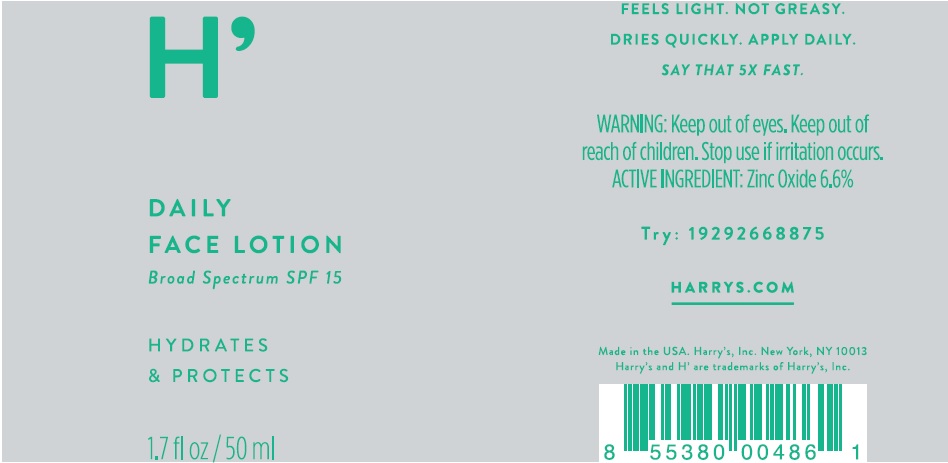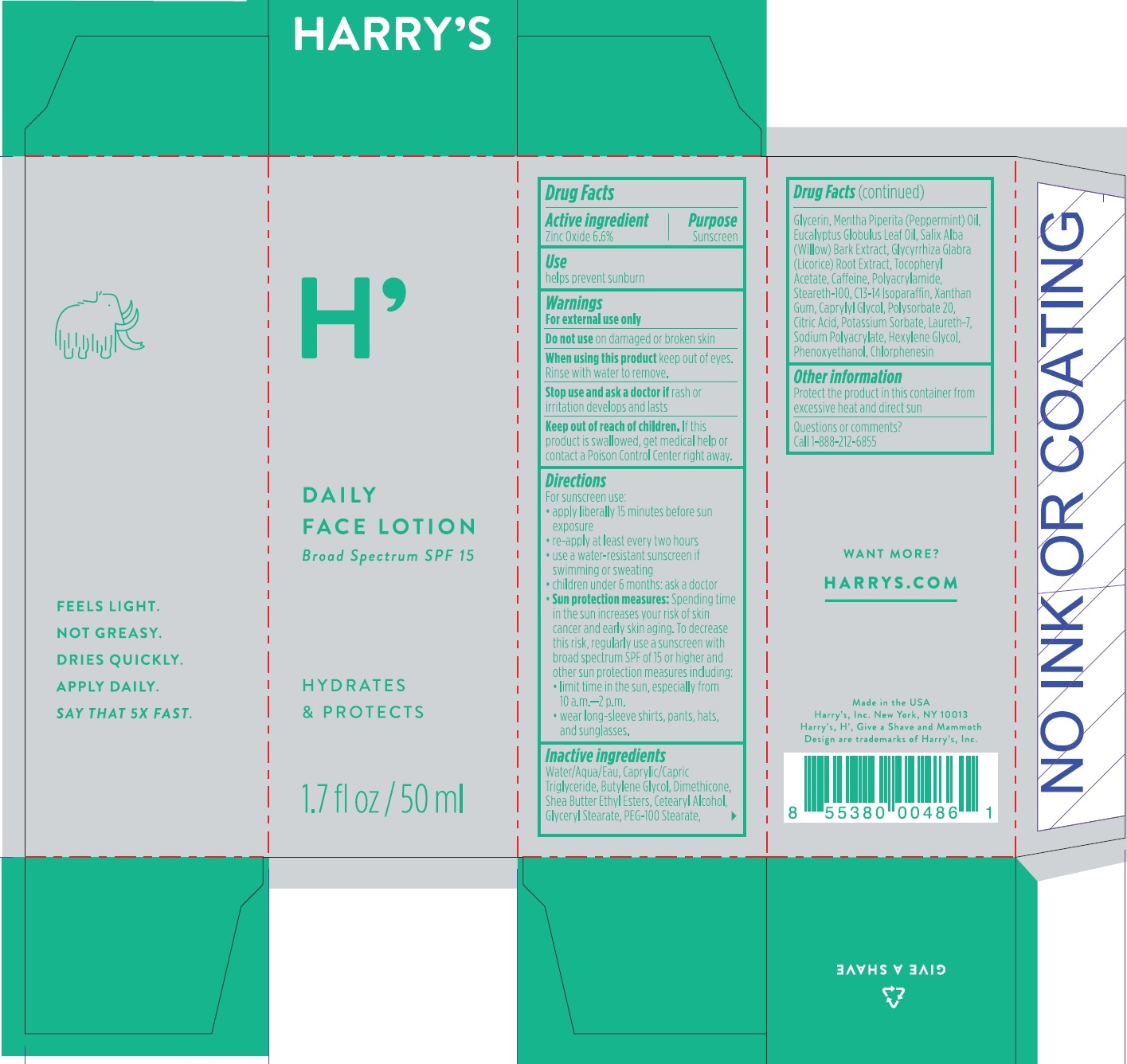 DRUG LABEL: Daily Face Broad Spectrum
NDC: 70533-001 | Form: LOTION
Manufacturer: Harry's, Inc.
Category: otc | Type: HUMAN OTC DRUG LABEL
Date: 20160404

ACTIVE INGREDIENTS: ZINC OXIDE 66 mg/1 mL
INACTIVE INGREDIENTS: WATER; MEDIUM-CHAIN TRIGLYCERIDES; DIMETHICONE; CETOSTEARYL ALCOHOL; GLYCERYL MONOSTEARATE; PEG-100 STEARATE; GLYCERIN; PEPPERMINT OIL; SALIX ALBA BARK; GLYCYRRHIZA GLABRA; .ALPHA.-TOCOPHEROL ACETATE; CAFFEINE; STEARETH-100; C13-14 ISOPARAFFIN; XANTHAN GUM; CAPRYLYL GLYCOL; POLYSORBATE 20; CITRIC ACID MONOHYDRATE; POTASSIUM SORBATE; LAURETH-7; HEXYLENE GLYCOL; PHENOXYETHANOL; CHLORPHENESIN

Daily Face Lotion - Broad Spectrum SPF 15

Active ingredient

Zinc Oxide 6.6%

Purpose

Sunscreen

Use

helps prevent sunburn

Warnings

For external use only

Do not use

on damaged or broken skin

When using this product

keep out of eyes. Rinse with water to remove.

Stop use and ask a doctor if

rash or irritation develops and lasts

Keep out of reach of children.

If this product is swallowed, get medical help or contact a Poison Center right away.

Directions

For sunscreen use:

• apply liberally 15 minutes before sun exposure

• re-apply at least every two hours

• use a water-resistant sunscreen if swimming or sweating

• children under 6 months: ask a doctor

• Sun protection measures: Spending time in the sun increases your risk of skin cancer and early skin aging. To decrease this risk, regularly use a sunscreen with broad spectrum SPF of 15 or higher and other sun protection measures including:

•limit time in the sun, especially from 10 a.m.

• wear long-sleeve shirts, pants, hats, and sunglasses.

Inactive ingredients

water/Aqua/Eau, Caprylic/Capric Triglyceride, Butylene Glycol, Dimethicone, Shea Butter Ethyl Esters, Cetearyl Alcohol, Glyceryl Stearate, PEG-100 Stearate, Glycerin, Mentha Piperita (Peppermint) Oil , Eucalyptus Globulus Leaf Oil, Salix Alba (Willow) Bark Extract, Glycyrrhiza Glabra (Licorice) Root Extract, Tocopheryl Acetate, Caffeine, Polyacrylamide, Streareth-100, C13-14 Isoparaffin, Xanthan Gum, Caprylyl Glycol, Polysorbate 20, Citric Acid, Potassium Sorbate, Laureth-7, Sodium Polyacrylate, Hexylene Glycol, Phenoxyethanol, Chlorphenesin

Other information

Protect the product in this container from excessive heat and direct sun

Questions or comments?

Call 1-888-212-6855